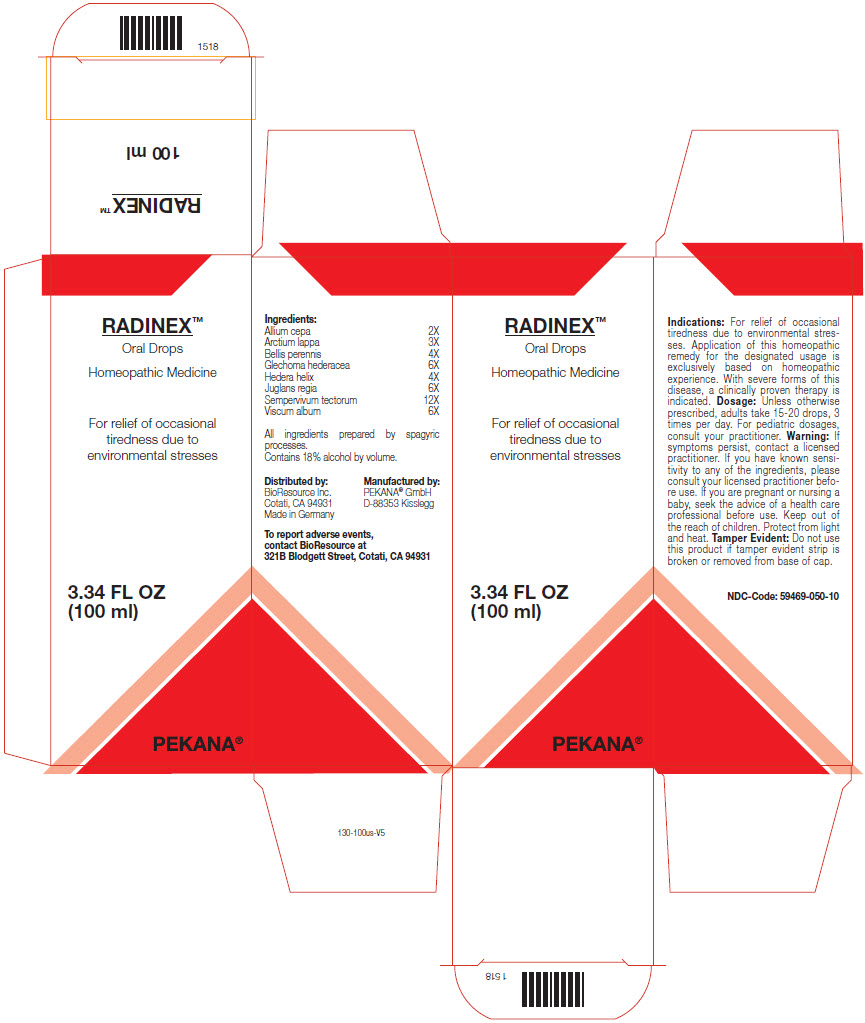 DRUG LABEL: RADINEX
NDC: 59469-050 | Form: SOLUTION/ DROPS
Manufacturer: PEKANA Naturheilmittel GmbH
Category: homeopathic | Type: HUMAN OTC DRUG LABEL
Date: 20221222

ACTIVE INGREDIENTS: Onion 2 [hp_X]/100 mL; Arctium lappa Root 3 [hp_X]/100 mL; BELLIS PERENNIS WHOLE 4 [hp_X]/100 mL; Glechoma hederacea Flowering Top 6 [hp_X]/100 mL; Hedera helix Flowering Twig 4 [hp_X]/100 mL; Juglans regia Whole 6 [hp_X]/100 mL; Sempervivum tectorum Leaf 12 [hp_X]/100 mL; Viscum album Fruiting Top 6 [hp_X]/100 mL
INACTIVE INGREDIENTS: Water; Alcohol

RADINEX™

ACTIVE INGREDIENT

Ingredients:
Allium cepa | 2X
Arctium lappa | 3X
Bellis perennis | 4X
Glechoma hederacea | 6X
Hedera helix | 4X
Juglans regia | 6X
Sempervivum tectorum | 12X
Viscum album | 6X

All ingredients prepared by spagyric processes.

INACTIVE INGREDIENT

Contains 18% alcohol by volume.

Indications

PURPOSE

For relief of occasional tiredness due to environmental stresses. Application of this homeopathic remedy for the designated usage is exclusively based on homeopathic experience. With severe forms of this disease, a clinically proven therapy is indicated.

Dosage

Unless otherwise prescribed, adults take 15-20 drops, 3 times per day. For pediatric dosages, consult your practitioner.

Warning

If symptoms persist, contact a licensed practitioner. If you have known sensitivity to any of the ingredients, please consult your licensed practitioner before use. If you are pregnant or nursing a baby, seek the advice of a health care professional before use.

Keep out of the reach of children.

STORAGE AND HANDLING

Protect from light and heat.

Tamper Evident

Do not use this product if tamper evident strip is broken or removed from base of cap.

QUESTIONS

To report adverse events, contact BioResource at 321B Blodgett Street, Cotati, CA 94931

Distributed by:
BioResource Inc.
Cotati, CA 94931

Manufactured by:
PEKANA® GmbH
D-88353 Kisslegg

PRINCIPAL DISPLAY PANEL - 100 ml Bottle Box

RADINEX™
Oral Drops

Homeopathic Medicine

For relief of occasional
tiredness due to
environmental stresses

3.34 FL OZ
(100 ml)

PEKANA®